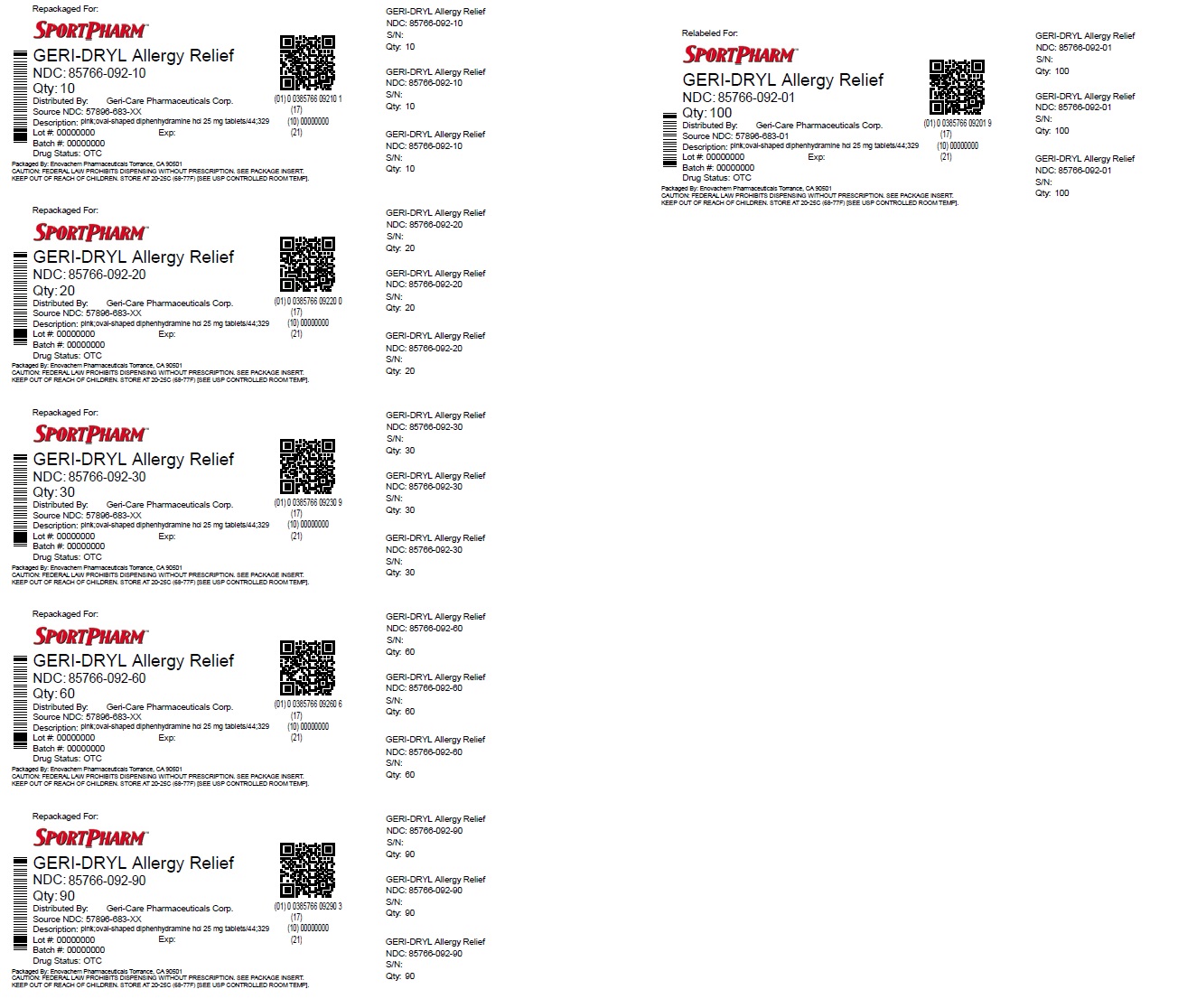 DRUG LABEL: Geri-Dryl allergy relief
NDC: 85766-092 | Form: TABLET, COATED
Manufacturer: Sportpharm, Inc. dba Sportpharm
Category: otc | Type: HUMAN OTC DRUG LABEL
Date: 20251008

ACTIVE INGREDIENTS: DIPHENHYDRAMINE HYDROCHLORIDE 25 mg/1 1
INACTIVE INGREDIENTS: STEARIC ACID; POLYVINYL ALCOHOL, UNSPECIFIED; STARCH, CORN; CALCIUM PHOSPHATE, DIBASIC, ANHYDROUS; SILICON DIOXIDE; D&C RED NO. 27; CELLULOSE, MICROCRYSTALLINE; MAGNESIUM STEARATE; POLYETHYLENE GLYCOL, UNSPECIFIED; TITANIUM DIOXIDE; TALC

Active ingredient (in each tablet)

Diphenhydramine Hydrochloride 25mg

Purpose

Antihistamine

Uses

- temporarily relieves these symptoms due to hay fever and other upper respiratory allergies:
- runny nose

- sneezing

- itching of the nose and throat
- itchy, watery eyes

Warnings

Do not use

- to make a child sleepy
- with any other product containing diphenhydramine, even one used on skin

Ask a doctor before use if you have

- a breathing problem such as chronic bronchitis or emphysema
- trouble urinating due to an enlarged prostate gland
- glaucoma

Ask a doctor or pharmacist before use if you aretaking sedatives or tranquilizers

When using this product

- excitability may occur, especially in children
- marked drowsiness may occur
- avoid alcoholic beverages
- alcohol, sedatives and tranquilizers may increase drowsiness
- use caution when driving a motor vehicle or operating machinery

If pregnant or breast-feeding,ask a health professional before use.

Keep out of reach of children.In case of overdose, get medical help or contact a Poison Control Center right away.

Directions

- do not exceed recommended dose
- adults and children 12 years and over, take 1 to 2 tablets every 4-6 hours, as needed; not more than 12 tablets in 24 hours, or as directed by a doctor
- children under 12 years: ask a doctor

Other information

- each tablet contains: calcium 30 mg
- store at 20-25°C (68-77°F); excursions permitted between 15°C - 30°C (59°F - 86°F)
- protect from moisture • Tamper Evident: Do not use if imprinted seal under cap is missing or broken.

Inactive ingredients

cellulose, D&C red #27 lake, dicalcium phosphate, magnesium stearate, PEG, polyvinyl alcohol, silica, starch, stearic acid, talc, titanium dioxide

Questions or comments?

1-800-540-3765